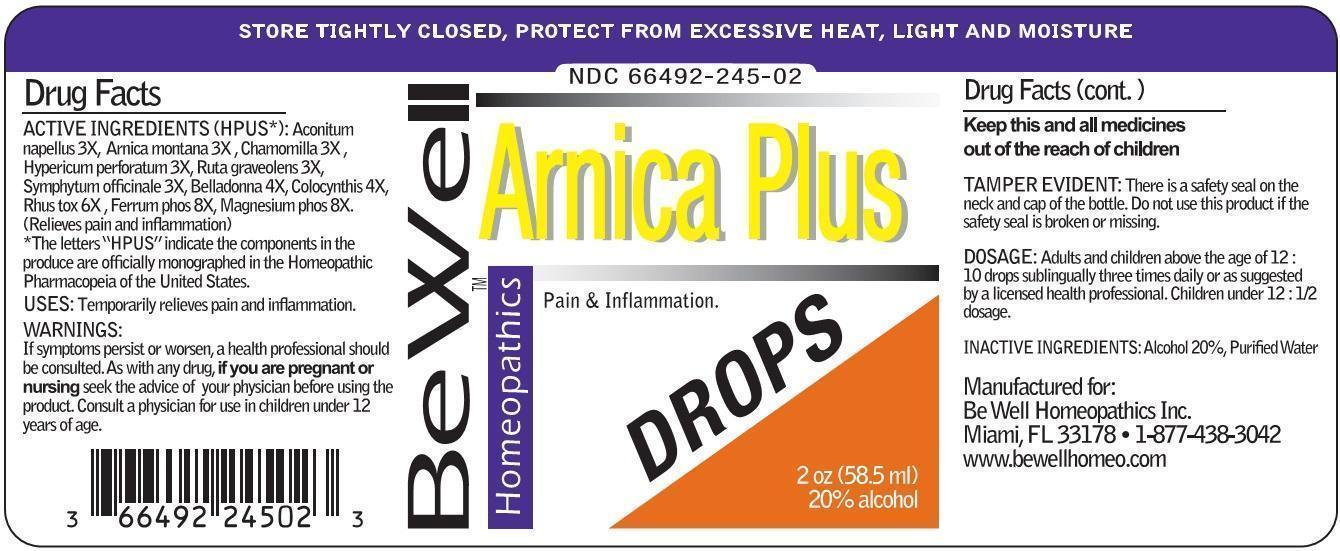 DRUG LABEL: Arnica Plus DROPS
NDC: 66492-245 | Form: LIQUID
Manufacturer: Be Well Medical dba Richard Clement Nutrition y Be Well Homeopathics
Category: homeopathic | Type: HUMAN OTC DRUG LABEL
Date: 20211229

ACTIVE INGREDIENTS: ACONITUM NAPELLUS 3 [hp_X]/1 mL; ARNICA MONTANA 3 [hp_X]/1 mL; MATRICARIA RECUTITA 3 [hp_X]/1 mL; HYPERICUM PERFORATUM 3 [hp_X]/1 mL; RUTA GRAVEOLENS FLOWERING TOP 3 [hp_X]/1 mL; COMFREY ROOT 3 [hp_X]/1 mL; ATROPA BELLADONNA 4 [hp_X]/1 mL; CITRULLUS COLOCYNTHIS FRUIT PULP 4 [hp_X]/1 mL; TOXICODENDRON PUBESCENS LEAF 6 [hp_X]/1 mL; FERROSOFERRIC PHOSPHATE 8 [hp_X]/1 mL; MAGNESIUM PHOSPHATE, DIBASIC 8 [hp_X]/1 mL
INACTIVE INGREDIENTS: WATER; ALCOHOL

Arnica Plus DROPS

ACTIVE INGREDIENT

ACTIVE INGREDIENTS (HPUS*): Aconitum napellus 3X, Arnica montana 3X, Chamomilla 3X, Hypericum perforatum 3X, Ruta graveolens 3X, Symphytum officinale 3X, Belladonna 4X, Colocynthis 4X, Rhus tox 6X, Ferrum phos 8X, Magnesium phos 8X. (Relieves pain and inflammation)

*The letters "HPUS" indicate the components in the produce are officially monographed in the Homeopathic Pharmacopeia of the United States.

INDICATIONS AND USAGE

USES: Temporarily relieves pain and inflammation.

WARNINGS:

If symptoms persist or worsen, a health professional should be consulted. As with any drug, if you are pregnant or nursing seek the advice of your physician before using the product. Consult a physician for use in children under 12 years of age.

KEEP OUT OF REACH OF CHILDREN

Keep this and all medicines out of the reach of children

OTHER SAFETY INFORMATION

TAMPER EVIDENT: There is a safety seal on the neck and cap of the bottle. Do not use this product if the safety seal is broken or missing.

STORE TIGHTLY CLOSED, PROTECT FROM EXCESSIVE HEAT, LIGHT AND MOISTURE

DOSAGE AND ADMINISTRATION

DOSAGE: Adults and children above the age of 12: 10 drops sublingually three times daily or as suggested by a licensed health professional. Children under 12: 1/2 dosage.

INACTIVE INGREDIENTS: Alcohol 20%, Purified Water.

QUESTIONS

Manufactured for:

Be Well Homeopathics Inc.

Miami, FL 33178

1-877-438-3042

www.bewellhomeo.com

PACKAGE LABEL

NDC 66492-245-02

Be Well HomeopathicsTM

Arnica Plus DROPS

Pain & Inflammation.

2oz (58.5 ml)

20% Alcohol

PURPOSE

Pain & Inflammation.